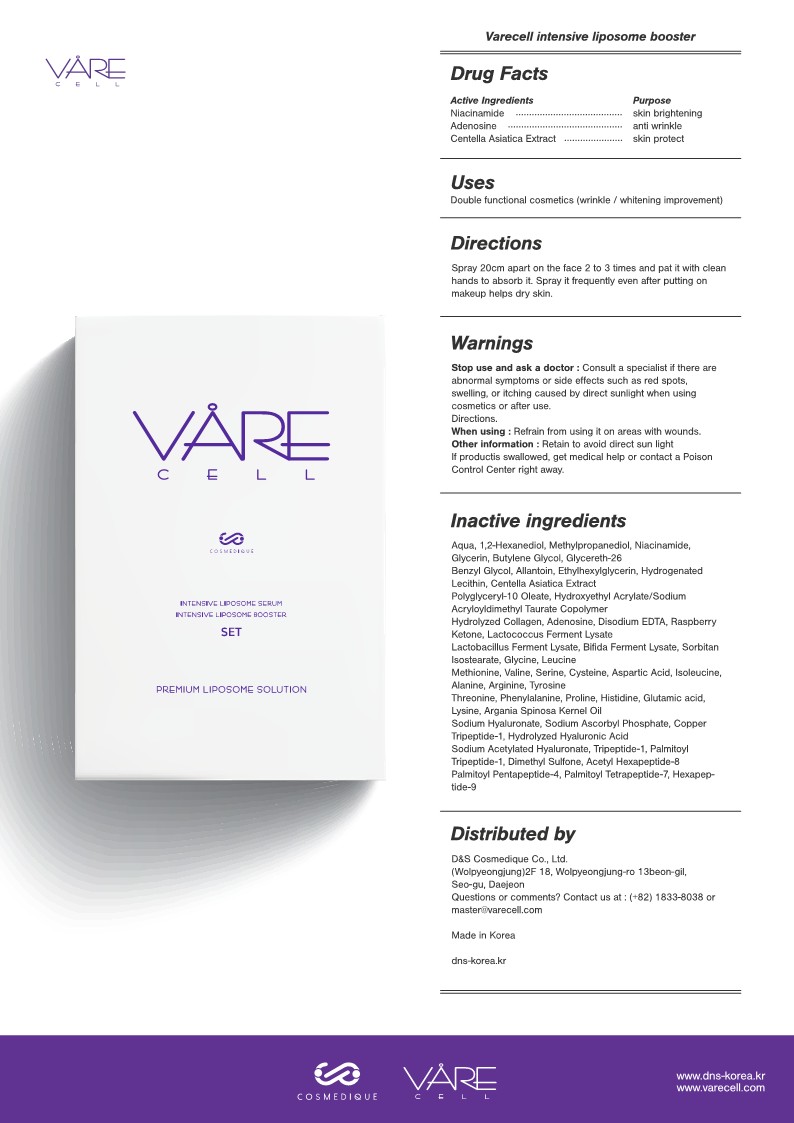 DRUG LABEL: Varecell Intensive Liposome Booster
NDC: 82190-103 | Form: LIQUID
Manufacturer: D&S Cosmedique Co.Ltd
Category: otc | Type: HUMAN OTC DRUG LABEL
Date: 20210903

ACTIVE INGREDIENTS: NIACINAMIDE 2 g/100 mL; CENTELLA ASIATICA WHOLE 89.53 g/100 mL; ADENOSINE 0.04 g/100 mL
INACTIVE INGREDIENTS: WATER; 1,2-HEXANEDIOL; METHYLPROPANEDIOL; BUTYLENE GLYCOL; GLYCERETH-26; HYDROGENATED SOYBEAN LECITHIN; ARGAN OIL; SODIUM ACETYLATED HYALURONATE; ACETYL HEXAPEPTIDE-8; PALMITOYL TETRAPEPTIDE-7; GLYCERIN; ALLANTOIN; ETHYLHEXYLGLYCERIN; POLYGLYCERYL-10 CAPRATE; COLLAGEN ALPHA-1(I) CHAIN BOVINE; EDETATE DISODIUM ANHYDROUS; BIFIDOBACTERIUM LONGUM; GLYCINE; VALINE; CYSTEINE; ASPARTIC ACID; TYROSINE; PHENYLALANINE; GLUTAMIC ACID; LYSINE; HEXAPEPTIDE-9; PREZATIDE COPPER; HYALURONIC ACID; PALMITOYL TRIPEPTIDE-1; DIMETHYL SULFONE; PALMITOYL PENTAPEPTIDE-4; PROLINAL; HISTIDINE; SODIUM POLYACRYLATE (2500000 MW); ETHYLENE GLYCOL MONOBENZYL ETHER; HYDROXYETHYL ACRYLATE/SODIUM ACRYLOYLDIMETHYL TAURATE COPOLYMER (45000 MPA.S AT 1%); 4-(P-HYDROXYPHENYL)-2-BUTANONE; LACTOCOCCUS LACTIS; SORBITAN ISOSTEARATE; LEUCINE; METHIONINE; SERINE; ISOLEUCINE; ALANINE; ARGININE; THREONINE

82190-103 Varecell Intensive Liposome Booster

Purpose

Skin Brightening, Anti-wrinkle

Use(s)

Double functional cosmetics (wrinkle / whitening improvement)

stop Use and Ask a Doctor

If abnormal symptoms or side effects such as red spots, swelling, or itching caused by direct sunlight when using cosmetics or after use

When using

Refrain from using it on areas with wounds.

Warnings: Other Information

Avoid direct sunlight when using or after use of the product.
If product is swallowed, get medical help or contact a Poison Control Center right away.

Keep out of reach of children

Directions

Spray 20cm apart on the face 2 to 3 times and pat it with clean hands to absorb it. Spray it frequently even after putting on makeup helps dry skin

Active Ingredients

Niacinamide, Adenosine, Centella Asiatica Extract

Inactive Ingredients

Aqua
1,2-Hexanediol
Methylpropanediol
Niacinamide
Glycerin
Butylene Glycol
Glycereth-26
Benzyl Glycol
Allantoin
Ethylhexylglycerin
Hydrogenated Lecithin
Centella Asiatica Extract
Polyglyceryl-10 Oleate
Hydroxyethyl Acrylate/Sodium Acryloyldimethyl Taurate Copolymer
Hydrolyzed Collagen
Adenosine
Disodium EDTA
Raspberry Ketone
Lactococcus Ferment Lysate
Lactobacillus Ferment Lysate
Bifida Ferment Lysate
Sorbitan Isostearate
Glycine
Leucine
Methionine
Valine
Serine
Cysteine
Aspartic Acid
Isoleucine
Alanine
Arginine
Tyrosine
Threonine
Phenylalanine
Proline
Histidine
Glutamic acid
Lysine
Argania Spinosa Kernel Oil
Sodium Hyaluronate
Sodium Ascorbyl Phosphate
Copper Tripeptide-1
Hydrolyzed Hyaluronic Acid
Sodium Acetylated Hyaluronate
Tripeptide-1
Palmitoyl Tripeptide-1
Dimethyl Sulfone
Acetyl Hexapeptide-8
Palmitoyl Pentapeptide-4
Palmitoyl Tetrapeptide-7
Hexapeptide-9

Package Label

82190-103